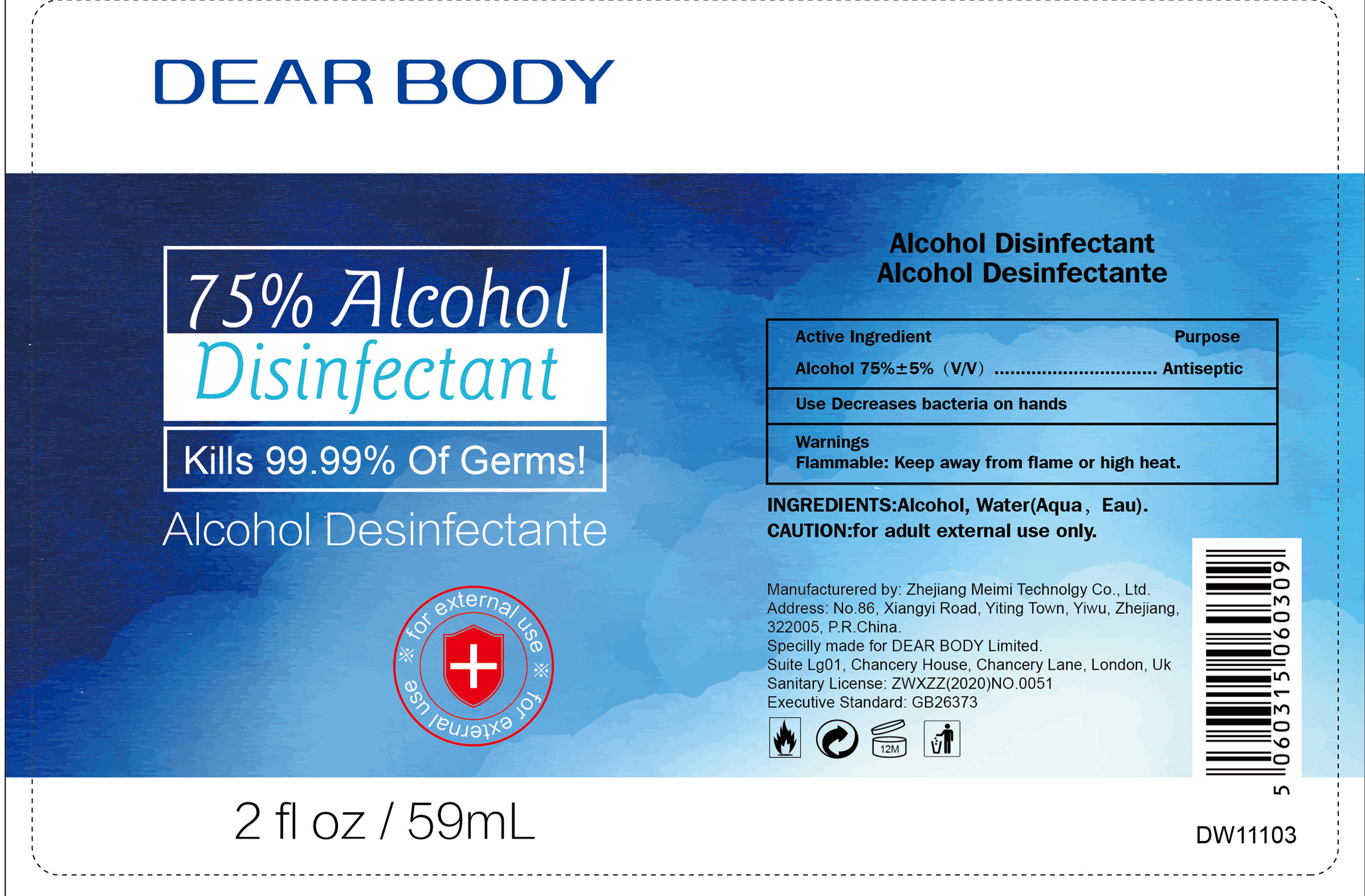 DRUG LABEL: Alcohol Disinfectant
NDC: 41366-010 | Form: LIQUID
Manufacturer: Zhejiang Meimi Technology Co., Ltd.
Category: otc | Type: HUMAN OTC DRUG LABEL
Date: 20200422

ACTIVE INGREDIENTS: ALCOHOL 44.84 mL/59 mL
INACTIVE INGREDIENTS: WATER

DOSAGE AND ADMINISTRATION

Keep away from flame or high heat.

INACTIVE INGREDIENT

Water

INDICATIONS AND USAGE

Put it on your hand with a bit, rub your hands together

ACTIVE INGREDIENT

alcohol

keep out of children

PURPOSE

Disinfection
Sterilization

WARNINGS

Keep away from flame or high heat.